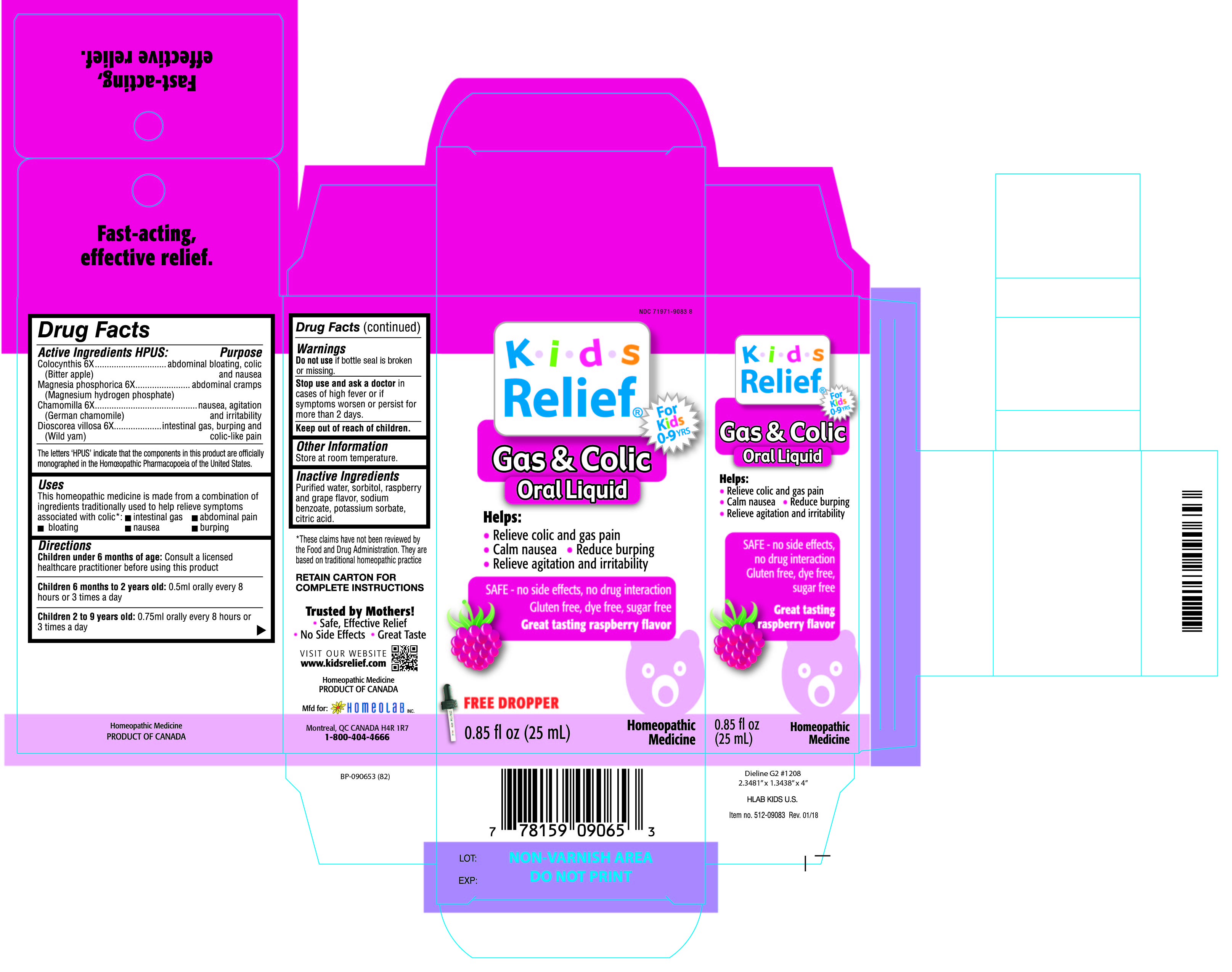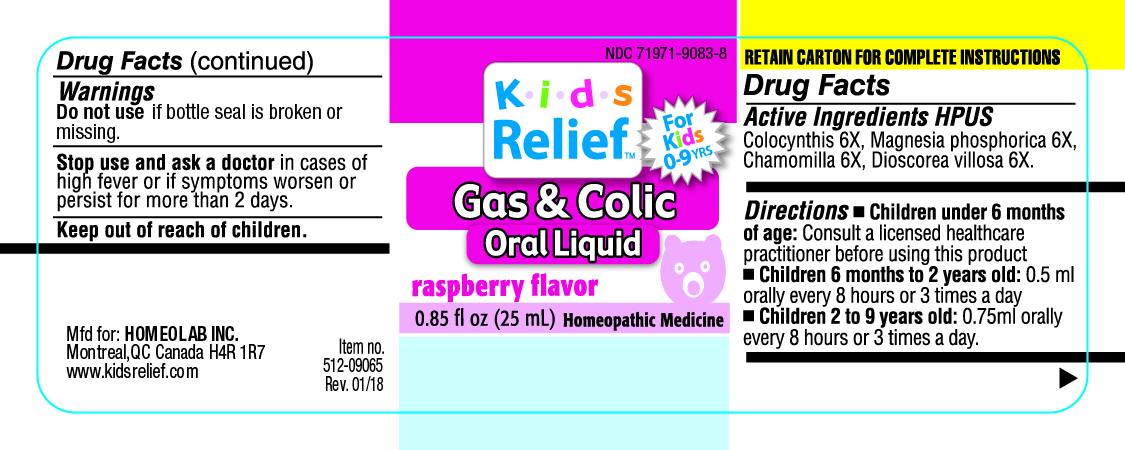 DRUG LABEL: Kids Relief
NDC: 71971-9083 | Form: LIQUID
Manufacturer: Homeolab International (Canada) inc
Category: homeopathic | Type: HUMAN OTC DRUG LABEL
Date: 20190716

ACTIVE INGREDIENTS: CITRULLUS COLOCYNTHIS FRUIT PULP 6 [hp_X]/25 mL; MAGNESIUM PHOSPHATE, DIBASIC TRIHYDRATE 6 [hp_X]/25 mL; MATRICARIA CHAMOMILLA 6 [hp_X]/25 mL; DIOSCOREA VILLOSA TUBER 6 [hp_X]/25 mL
INACTIVE INGREDIENTS: WATER; SORBITOL; SODIUM BENZOATE; POTASSIUM SORBATE; CITRIC ACID ACETATE

Active Ingredients HPUS:

Colocynthis 6X

(Bitter apple)

Magnesia phosphorica 6X

(Magnesium hydrogen phosphate)

Chamomilla 6X

(German chamomille)

Dioscorea villosa 6X

(Wild yam)

The letters 'HPUS' indicate that the component in this product is officially

monographed in the Homeopathic Pharmacopoeia of the United States)

Purpose

Colocynthis 6X...........................................abdominal bloating, colic and nausea

(Bitter apple)

Magnesia phosphorica 6X ----------------------abdominal cramps

(Magnesium hydrogen phosphate)

Chamomilla 6X ..........................................nausea, agitation and irritability

(German chamomille)

Dioscorea villosa 6X ...................................intestinal gas, burping and colic-like pain

(Wild yam)

Uses

This homeopathic medicine is made from a combination of

ingredients traditionally used to help relieve symptoms

associated with colic* •intestinal gas •abdominal pain

•bloating •nausea •burping

Directions

Children udner 6 months of age: consult a licensed

healthcare practitioner before using this product

Children 6 months to 2 years old: 0.5 ml orally every 8

hours or 3 times a day

Children 2 to 9 years old: 0.75 ml orally every 8 hours or

3 times a day

Warnings

Do not use if bottle seal is broken

or missing,

Stop use and ask a doctor in cases of high fever or if

symptoms worsen or persist for

more than 2 days.

Keep out of reach of children.

Other information

Store at room temperature

Inactive Ingredients

Purified water, sorbitol, raspberry

and grape flavor, sodium

benzoate, potassium sorbate,

citric acid.